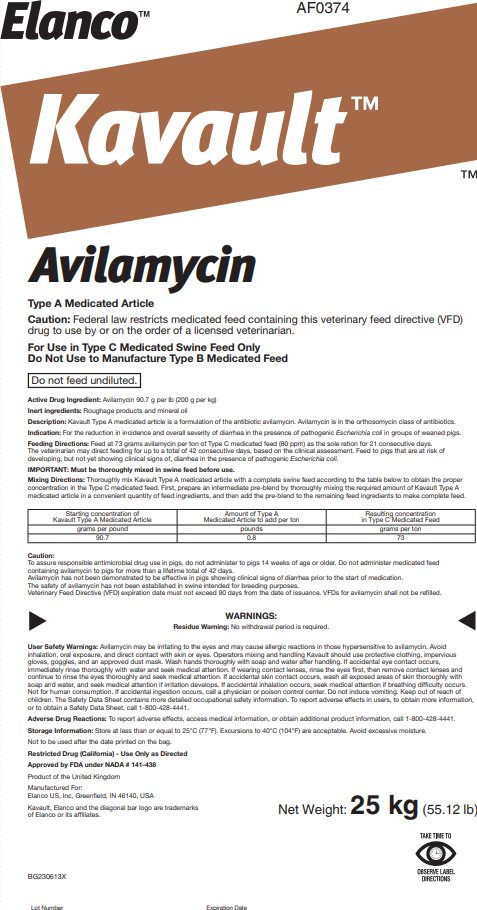 DRUG LABEL: Kavault
NDC: 58198-0374 | Form: POWDER
Manufacturer: Elanco US Inc.
Category: animal | Type: VFD TYPE A MEDICATED ARTICLE ANIMAL DRUG LABEL
Date: 20251121

ACTIVE INGREDIENTS: avilamycin 200 g/1 kg

Elanco™
AF0374
Kavault™
Avilamycin

Type A Medicated Article

Caution:

Federal law restricts medicated feed containing this veterinary feed directive (VFD) drug to use by or on the order of a licensed veterinarian.

For Use in Type C Medicated Swine Feed Only
Do Not Use to Manufacture Type B Medicated Feed

Do not feed undiluted.

Active Drug Ingredient:

Avilamycin 90.7 g per lb (200 g per kg)

Inert ingredients:

Roughage products and mineral oil

Description:

Kavault Type A medicated article is a formulation of the antibiotic avilamycin. Avilamycin is in the orthosomycin class of antibiotics.

Indication:

For the reduction in incidence and overall severity of diarrhea in the presence of pathogenic Escherichia coli in groups of weaned pigs.

Feeding Directions:

Feed at 73 grams avilamycin per ton of Type C medicated feed (80 ppm) as the sole ration for 21 consecutive days. The veterinarian may direct feeding for up to a total of 42 consecutive days, based on the clinical assessment. Feed to pigs that are at risk of developing, but not yet showing clinical signs of, diarrhea in the presence of pathogenic Escherichia coli.

IMPORTANT: Must be thoroughly mixed in swine feed before use.

Mixing Directions:

Thoroughly mix Kavault Type A medicated article with a complete swine feed according to the table below to obtain the proper concentration in the Type C medicated feed. First, prepare an intermediate pre-blend by thoroughly mixing the required amount of Kavault Type A medicated article in a convenient quantity of feed ingredients, and then add the pre-blend to the remaining feed ingredients to make complete feed.

Starting concentration of Kavault Type A Medicated Article | Amount of Type A Medicated Article to add per ton | Resulting concentration in Type C Medicated Feed
grams per pound | pounds | grams per ton
90.7 | 0.8 | 73

Caution:

To assure responsible antimicrobial drug use in pigs, do not administer to pigs 14 weeks of age or older. Do not administer medicated feed containing avilamycin to pigs for more than a lifetime total of 42 days.

Avilamycin has not been demonstrated to be effective in pigs showing clinical signs of diarrhea prior to the start of medication.

The safety of avilamycin has not been established in swine intended for breeding purposes.

Veterinary Feed Directive (VFD) expiration date must not exceed 90 days from the date of issuance. VFDs for avilamycin shall not be refilled.

WARNINGS:

Residue Warning: No withdrawal period is required.

User Safety Warnings: Avilamycin may be irritating to the eyes and may cause allergic reactions in those hypersensitive to avilamycin. Avoid inhalation, oral exposure, and direct contact with skin or eyes. Operators mixing and handling Kavault should use protective clothing, impervious gloves, goggles, and an approved dust mask. Wash hands thoroughly with soap and water after handling. If accidental eye contact occurs, immediately rinse thoroughly with water and seek medical attention. If wearing contact lenses, rinse the eyes first, then remove contact lenses and continue to rinse the eyes thoroughly and seek medical attention. If accidental skin contact occurs, wash all exposed areas of skin thoroughly with soap and water, and seek medical attention if irritation develops. If accidental inhalation occurs, seek medical attention if breathing difficulty occurs. Not for human consumption. If accidental ingestion occurs, call a physician or poison control center. Do not induce vomiting. Keep out of reach of children. The Safety Data Sheet contains more detailed occupational safety information. To report adverse effects in users, to obtain more information, or to obtain a Safety Data Sheet, call 1-800-428-4441.

Adverse Drug Reactions: To report adverse effects, access medical information, or obtain additional product information, call 1-800-428-4441.

Storage Information:

Store at less than or equal to 25°C (77°F). Excursions to 40°C (104°F) are acceptable. Avoid excessive moisture.

Not to be used after the date printed on the bag.

Restricted Drug (California) - Use Only as Directed

Approved by FDA under NADA # 141-438

Product of the United Kingdom

Manufactured For:
Elanco US, Inc, Greenfield, IN 46140, USA
Kavault, Elanco and the diagonal bar logo are trademarks
of Elanco or its affiliates.

Net Weight: 25 kg (55.12 lb)

TAKE TIME TO
OBSERVE LABEL
DIRECTIONS

BG230613X

Principal Display Panel – 25 kg Bag Label

Elanco™ AF0374

Kavault™

Avilamycin